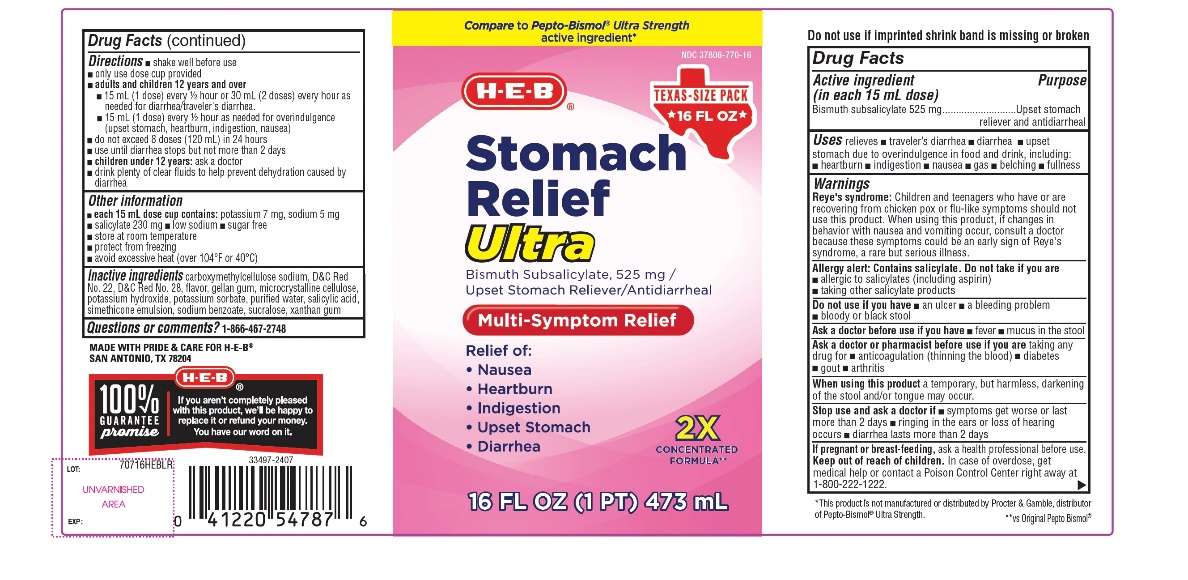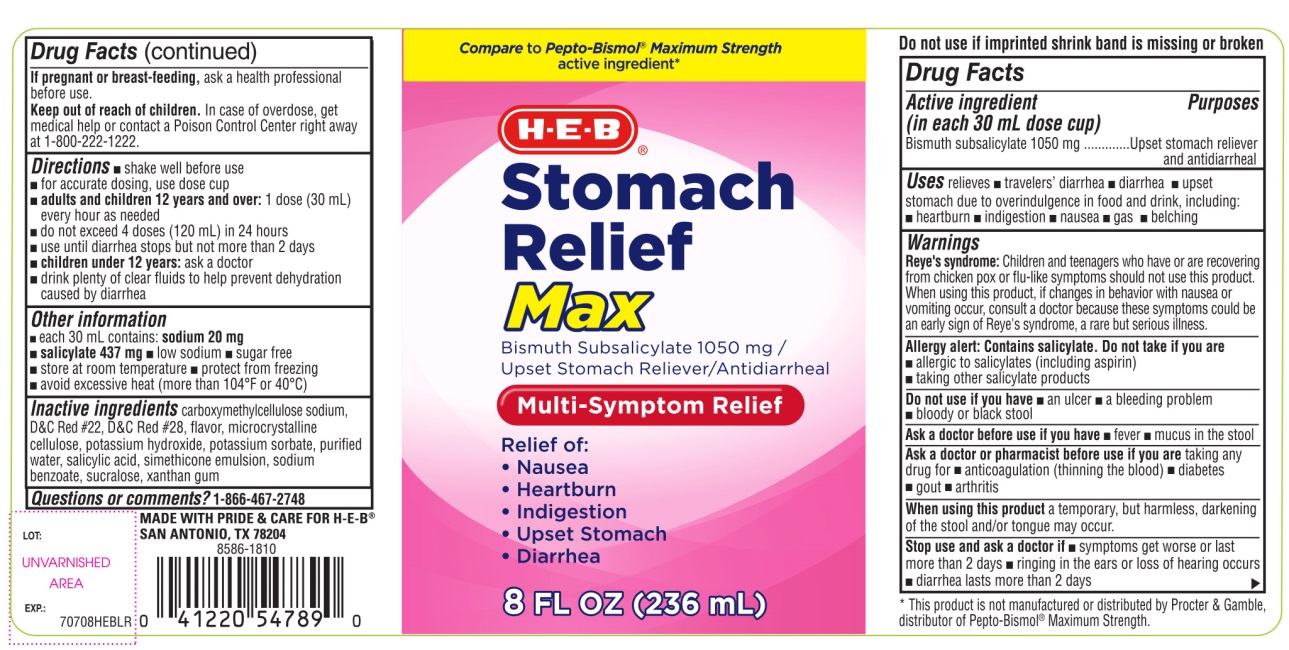 DRUG LABEL: HEB Stomach Relief

NDC: 37808-770 | Form: SUSPENSION
Manufacturer: HEB
Category: otc | Type: HUMAN OTC DRUG LABEL
Date: 20251003

ACTIVE INGREDIENTS: BISMUTH SUBSALICYLATE 1050 mg/30 mL
INACTIVE INGREDIENTS: CARBOXYMETHYLCELLULOSE SODIUM, UNSPECIFIED; D&C RED NO. 22; D&C RED NO. 28; MICROCRYSTALLINE CELLULOSE; POTASSIUM HYDROXIDE; POTASSIUM SORBATE; WATER; SALICYLIC ACID; DIMETHICONE, UNSPECIFIED; SODIUM BENZOATE; SUCRALOSE; XANTHAN GUM

HEB Max Strength Bismuth Subsalicylate Drug Facts

Active ingredient (in each 30 mL dose cup)

Bismuth subsalicylate 1050 mg

Purposes

Upset stomach reliever and antidiarrheal

Uses

relieves

- travelers’ diarrhea
- diarrhea
- upset stomach due to overindulgence in food and drink, including:
- heartburn
- indigestion
- nausea
- gas
- belching

Warnings

Reye’s syndrome:Children and teenagers who have or are recovering from chicken pox or flu-like symptoms should not use this product. When using this product, if changes in behavior with nausea and vomiting occur, consult a doctor because these symptoms could be an early sign of Reye’s syndrome, a rare but serious illness.

Allergy alert: Contains salicylate. Do not take if you are

- allergic to salicylates (including aspirin)
- taking other salicylate products

Do not use

if you have

- an ulcer
- a bleeding problem
- bloody or black stool

Ask a doctor before use if you have

- fever
- mucus in the stool

Ask a doctor or pharmacist before use if you are

taking any drug for

- anticoagulation (thinning the blood)
- diabetes
- gout
- arthritis

When using this product

a temporary, but harmless, darkening of the stool and/or tongue may occur

Stop use and ask a doctor if

- symptoms get worse or last more than 2 days
- ringing in the ears or loss of hearing occurs
- diarrhea lasts more than 2 days

If pregnant or breast-feeding,

ask a health professional before use.

Keep out of reach of children.

In case of overdose, get medical help or contact a Poison Control Center right away at (1-800-222-1222).

Directions

- shake well before use
- for accurate dosing use dose cup
- adults and children 12 years and over:1 dose (30 mL) every hour as needed
- do not exceed 4 doses (120 mL) in 24 hours
- use until diarrhea stops but not more than 2 days
- children under 12 years: ask a doctor
- drink plenty of clear fluids to help prevent dehydration caused by diarrhea

Other information

- each 30 mL contains: sodium 20 mg
- salicylate 437 mg
- low sodium
- sugar free
- store at room temperature.
- protect from freezing
- avoid excessive heat (more than 104°F or 40°C).

Inactive ingredients

carboxymethylcellulose sodium, D&C Red #22, D&C Red #28, flavor, microcrystalline cellulose, potassium hydroxide, potassium sorbate, purified water, salicylic acid, simethicone emulsion, sodium benzoate, sucralose, xanthan gum

Questions or comments?

1-866-467-2748

Principal Display Panel

*Compare to Pepto-Bismol® Maximum Strength active ingredient*

HEB®

Stomach Relief

Max

Bismuth Subsalicylate 1050 mg

Upset Stomach Reliever/Antidiarrheal

Multi-Symptom Relief

Relieves:

- Nausea
- Heartburn
- Indigestion
- Upset Stomach
- Diarrhea

MADE WITH PRIDE & CARE FOR H-E-B®

SAN ANTONIA, TX 78204

100% GUARANTEE promise, if you aren’t completely pleased with this product, we’ll be happy to replace it or refund your money. You have our word on it.

*This product is not manufactured or distributed by Procter & Gamble, distributor of Pepto-Bismol®Maximum Strength.

Package Label 473 mL